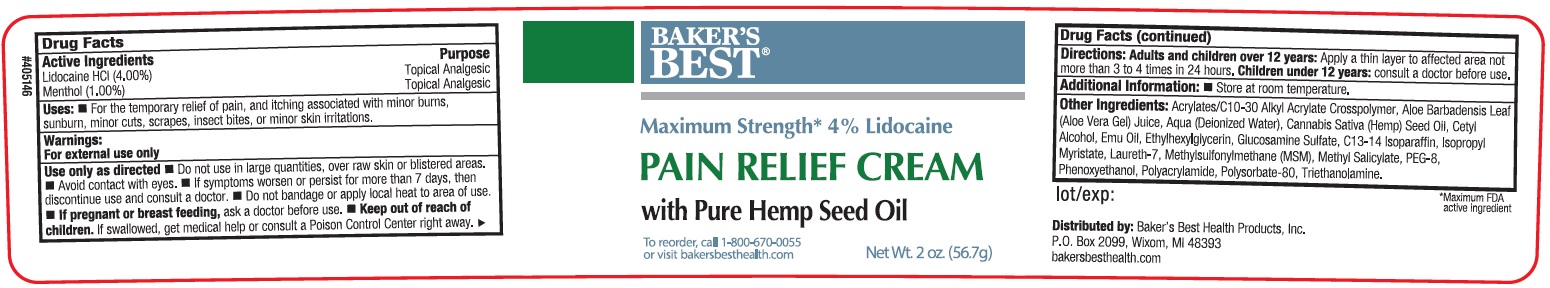 DRUG LABEL: BAKERS BEST Pain Relief with Pure Hemp Seed Oil
NDC: 76102-389 | Form: CREAM
Manufacturer: BAKER'S BEST HEALTH PRODUCTS, INC.
Category: otc | Type: HUMAN OTC DRUG LABEL
Date: 20231106

ACTIVE INGREDIENTS: LIDOCAINE HYDROCHLORIDE 40 mg/1 g; MENTHOL 10 mg/1 g
INACTIVE INGREDIENTS: ALOE VERA LEAF; WATER; CANNABIS SATIVA SEED OIL; CETYL ALCOHOL; EMU OIL; ETHYLHEXYLGLYCERIN; GLUCOSAMINE SULFATE; C13-14 ISOPARAFFIN; ISOPROPYL MYRISTATE; LAURETH-7; DIMETHYL SULFONE; METHYL SALICYLATE; POLYETHYLENE GLYCOL 400; PHENOXYETHANOL; POLYSORBATE 80; TROLAMINE

BAKER'S BEST Pain Relief Cream with Pure Hemp Seed Oil

Active Ingredients

Lidocaine HCl (4.00%)

Menthol (1.00%)

Purpose

Topical Analgesic

Uses:

- For the temporary relief of pain, and itching associated with minor burns, sunburn, minor cuts, scrapes, insect bites, or minor skin irritations.

Warnings:

For external use only

Use only as directed

Do not use

- in large quantities, over raw skin or blistered areas.
- Avoid contact with eyes.
- If symptoms worsen or persist for more than 7 days, then discontinue use and consult a doctor.
- Do not bandage or apply local heat to area of use.

If pregnant or breast feeding,

- ask a doctor before use,

Keep out of reach of children.

- If swallowed, get medical help or contact a Poison Control Center right away.

Directions:

Apply a thin layer to affected area not more than 3 to 4 times in 24 hours. Adults and children over 12 years:

consult a doctor before use. Children under 12 years:

Additional Information:

- Store at room temperature.

Other Ingredients:

Acrylates/C10-30 Alkyl Acrylate Crosspolymer, Aloe Barbadensis Leaf (Aloe Vera Gel) Juice, Aqua (Deionized Water), Cannabis Sativa (Hemp) Seed Oil, Cetyl Alcohol, Emu Oil, Ethylhexylglycerin, Glucosamine Sulfate, C13-14 Isoparaffin, Isopropyl Myristate, Laureth-7, Methylsulfonylmethane (MSM), Methyl Salicylate, PEG-8, Phenoxyethanol, Polyacrylamide, Polysorbate-80, Triethanolamine.